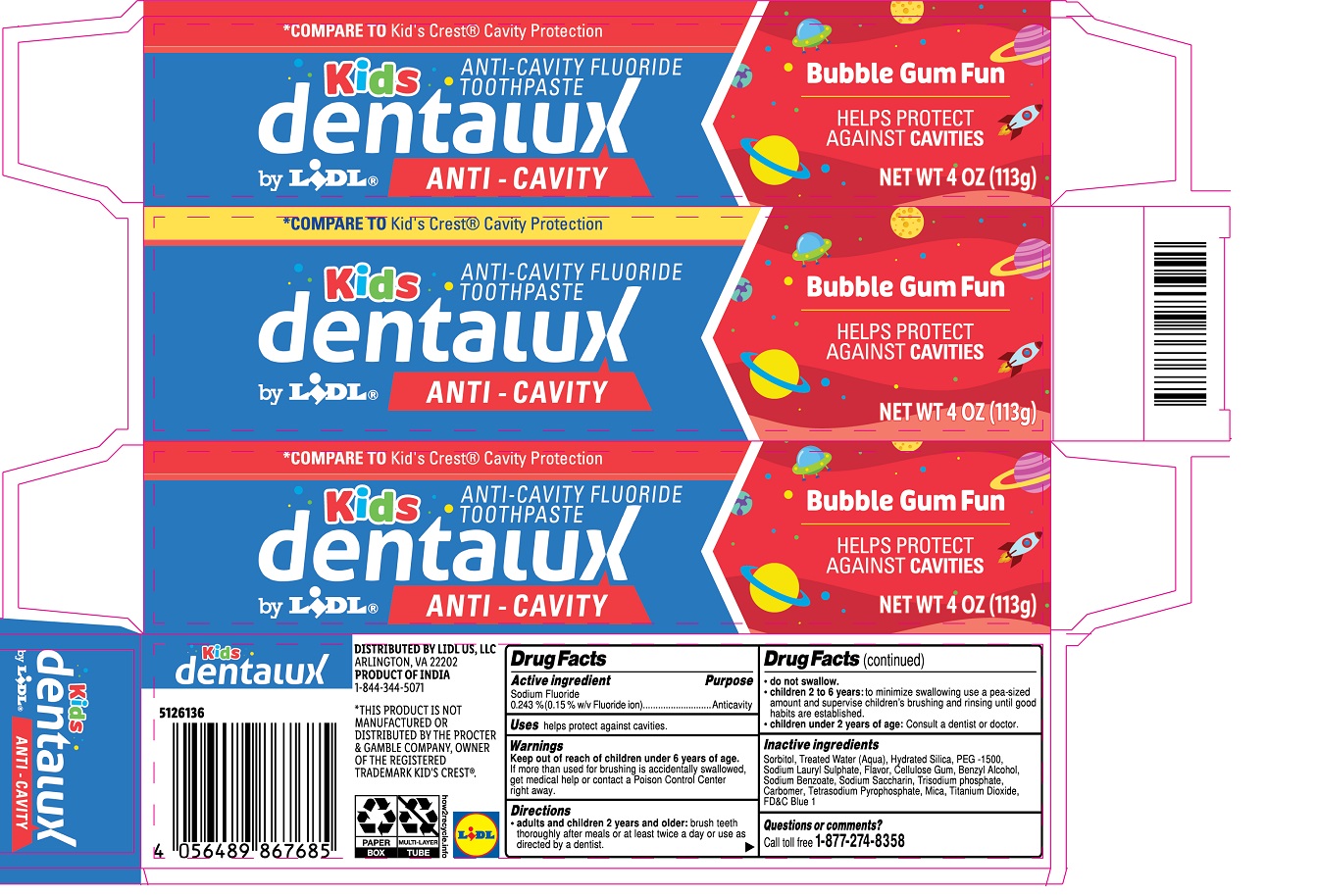 DRUG LABEL: dentalux Kids ANTI-CAVITY FLUORIDE Bubble Gum
NDC: 71141-184 | Form: PASTE, DENTIFRICE
Manufacturer: Lidl US, LLC
Category: otc | Type: HUMAN OTC DRUG LABEL
Date: 20240702

ACTIVE INGREDIENTS: SODIUM FLUORIDE 0.243 g/100 g
INACTIVE INGREDIENTS: SORBITOL; WATER; HYDRATED SILICA; POLYETHYLENE GLYCOL 1600; SODIUM LAURYL SULFATE; CARBOXYMETHYLCELLULOSE SODIUM, UNSPECIFIED; BENZYL ALCOHOL; SODIUM BENZOATE; SACCHARIN SODIUM; SODIUM PHOSPHATE, TRIBASIC, ANHYDROUS; CARBOMER HOMOPOLYMER, UNSPECIFIED TYPE; SODIUM PYROPHOSPHATE; MICA; TITANIUM DIOXIDE; FD&C BLUE NO. 1

dentalux Kids ANTI-CAVITY FLUORIDE TOOTHPASTE

Active ingredient

Sodium Fluoride
0.243 % (0.15 % w/v Fluoride ion)

Purpose

Anticavity

Uses

helps protect against cavities.

Warnings

Keep out of reach of children under 6 years of age. If more than used for brushing is accidentally swallowed, get medical help or contact a Poison Control Center right away.

Directions

• adults and children 2 years and older: brush teeth thoroughly after meals or at least twice a day or use as directed by a dentist.
• do not swallow.
• children 2 to 6 years: to minimize swallowing use a pea-sized amount and supervise children's brushing and rinsing until good habits are established.
• children under 2 years of age: Consult a dentist or doctor.

Inactive ingredients

Sorbitol, Treated Water (Aqua), Hydrated Silica, PEG-1500, Sodium Lauryl Sulphate, Flavor, Cellulose Gum, Benzyl Alcohol, Sodium Benzoate, Sodium Saccharin, Trisodium phosphate, Carbomer, Tetrasodium Pyrophosphate, Mica, Titanium Dioxide, FD&C Blue 1

Questions or comments?

Call toll free 1-877-274-8358

*COMPARE TO Kid's Crest® Cavity Protection

Bubble Gum Fun

HELPS PROTECT AGAINST CAVITIES

DISTRIBUTED BY LIDL US, LLC
ARLINGTON, VA 22202
PRODUCT OF INDIA
1-844-344-5071

*THIS PRODUCT IS NOT MANUFACTURED OR DISTRIBUTED BY THE PROCTER & GAMBLE COMPANY, OWNER OF THE REGISTERED TRADEMARK KID'S CREST®.